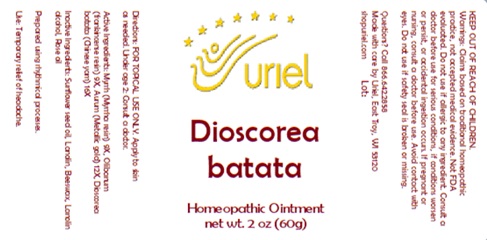 DRUG LABEL: Dioscorea batata
NDC: 48951-4198 | Form: OINTMENT
Manufacturer: Uriel Pharmacy, Inc
Category: homeopathic | Type: HUMAN OTC DRUG LABEL
Date: 20250819

ACTIVE INGREDIENTS: MYRRH 9 [hp_X]/1 g; CHINESE YAM 16 [hp_X]/1 g; GOLD 12 [hp_X]/1 g; FRANKINCENSE 9 [hp_X]/1 g
INACTIVE INGREDIENTS: SUNFLOWER OIL; ROSE OIL; LANOLIN; LANOLIN ALCOHOL; BEESWAX

Dioscorea batata

INDICATIONS AND USAGE

Directions: FOR TOPICAL USE ONLY.

DOSAGE AND ADMINISTRATION

Apply to skin as needed. Under age 2: Consult a doctor.

ACTIVE INGREDIENT

Active Ingredients: Myrrh (Myrrha resin) 9X, Olibanum (frankincense resin) 9X, Aurum (Metallic gold) 12X, Dioscorea batata (Chinese yam) 16X

INACTIVE INGREDIENT

Inactive Ingredients: Sunflower seed oil, Lanolin, Beeswax, Lanolin alcohol, Rose oil

Prepared using rhythmical processes.

PURPOSE

Use: Temporary relief of headache.

KEEP OUT OF REACH OF CHILDREN.

WARNINGS

Warnings: Claims based on traditional homeopathic practice, not accepted medical evidence. Not FDA evaluated. Do not use if allergic to any ingredient. Consult a doctor before use for serious conditions, if conditions worsen or persist, or accidental ingestion occurs. If pregnant or nursing, consult a doctor before use. Avoid contact with eyes. Do not use if safety seal is broken or missing.

Questions? Call 866.642.2858
Made with care by Uriel, East Troy, WI 53120
shopuriel.com Lot: